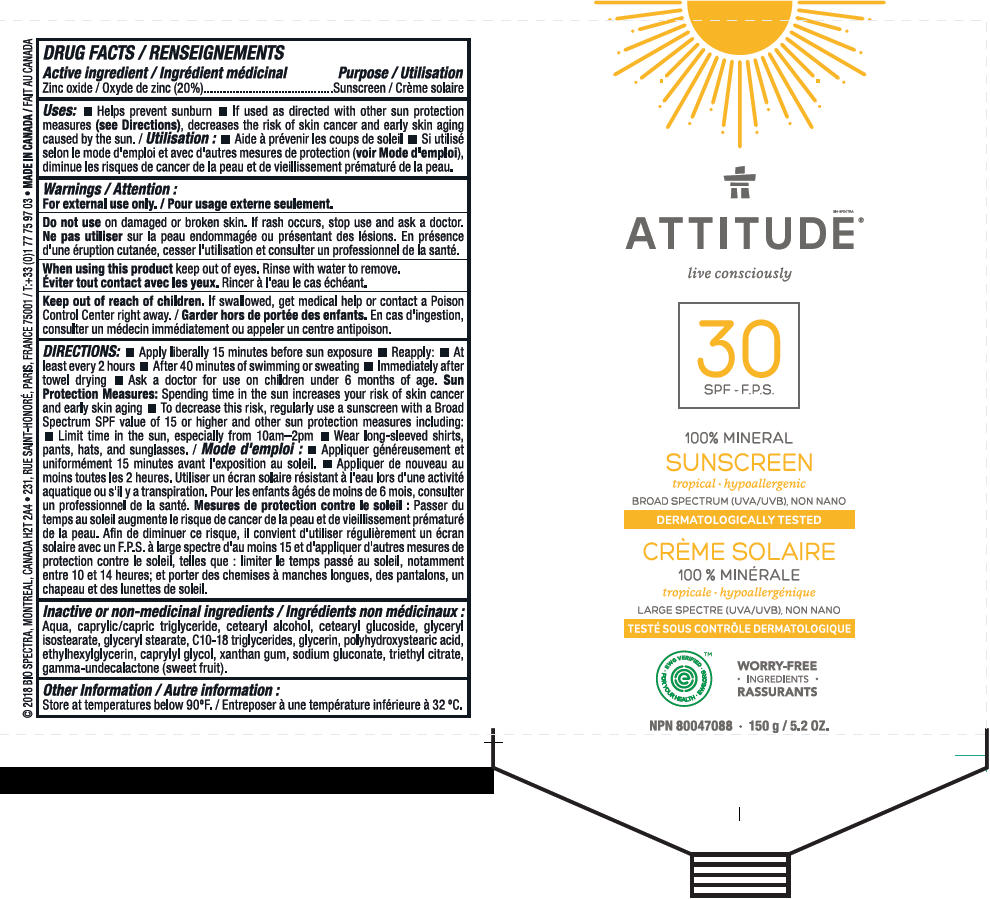 DRUG LABEL: ATTITUDE 
NDC: 61649-011 | Form: CREAM
Manufacturer: Bio Spectra
Category: otc | Type: HUMAN OTC DRUG LABEL
Date: 20180706

ACTIVE INGREDIENTS: ZINC OXIDE 20 g/100 g
INACTIVE INGREDIENTS: WATER; MEDIUM-CHAIN TRIGLYCERIDES; CETOSTEARYL ALCOHOL; CETEARYL GLUCOSIDE; GLYCERYL ISOSTEARATE; GLYCERYL MONOSTEARATE; C10-18 TRIGLYCERIDES; GLYCERIN; ETHYLHEXYLGLYCERIN; CAPRYLYL GLYCOL; POLYHYDROXYSTEARIC ACID (2300 MW); XANTHAN GUM; SODIUM GLUCONATE; TRIETHYL CITRATE; .GAMMA.-UNDECALACTONE; .GAMMA.-OCTALACTONE

ATTITUDE®
100% Mineral sunscreen - Tropical

DRUG FACTS:

Active ingredient

Zinc oxide (20%)

Purpose

Sunscreen

Uses

- Helps prevent sunburn
- If used as directed with other sun protection measures (see Directions), decreases the risk of skin cancer and early skin aging caused by the sun.

Warnings

For external use only. Do not use on damaged or broken skin. If rash occurs, stop use and ask a doctor. When using this product keep out of eyes. Rinse with water to remove.

Keep out of reach of children. If swallowed, get medical help or contact a Poison Control Center right away.

DIRECTIONS

- Apply liberally 15 minutes before sun exposure
- Reapply:
  - At least every 2 hours
  - After 40 minutes of swimming or sweating
  - Immediately after towel drying
- Ask a doctor for use on children under 6 months of age.

Sun Protection Measures: Spending time in the sun increases your risk of skin cancer and early skin aging

- To decrease this risk, regularly use a sunscreen with a Broad Spectrum SPF value of 15 or higher and other sun protection measures including:
  - Limit time in the sun, especially from 10am–2pm
  - Wear long-sleeved shirts, pants, hats, and sunglasses.

Inactive or non-medicinal ingredients

Aqua, caprylic/capric triglyceride, cetearyl alcohol, cetearyl glucoside, glyceryl isostearate, glyceryl stearate, C10-18 triglycerides, glycerin, polyhydroxystearic acid, ethylhexylglycerin, caprylyl glycol, xanthan gum, sodium gluconate, triethyl citrate, gamma-undecalactone (sweet fruit).

Other Information

Store at temperatures below 90oF.

PRINCIPAL DISPLAY PANEL - 150 g Tube Label

BIO SPECTRA
ATTITUDE®

live consciously

30
SPF

100% MINERAL
SUNSCREEN
tropical • hypoallergenic
BROAD SPECTRUM (UVA/UVB), NON NANO

DERMATOLOGICALLY TESTED

• EWG VERIFIED
FOR YOUR HEALTH •
EWG.ORG •™

WORRY-FREE
• INGREDIENTS •

NPN 80047088 • 150 g / 5.2 OZ.